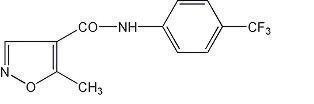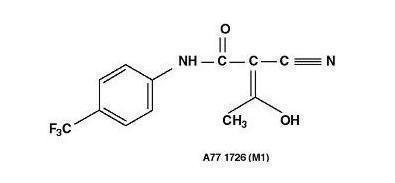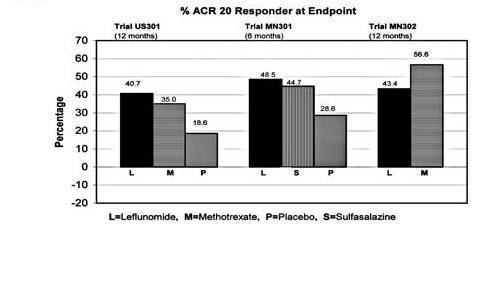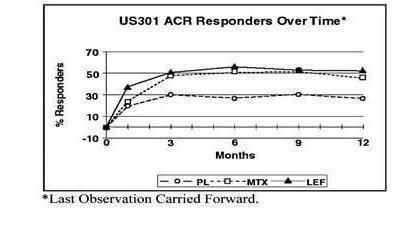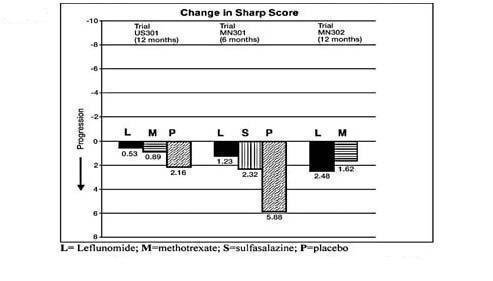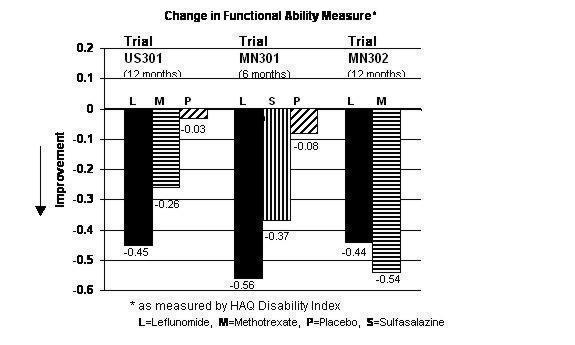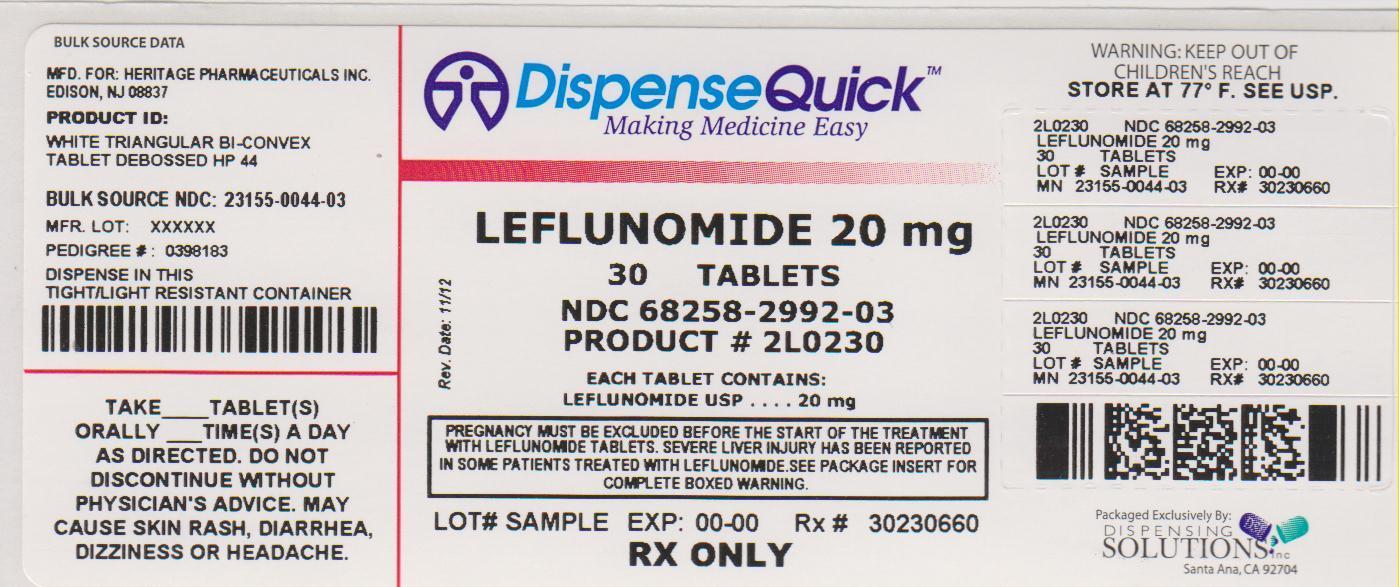 DRUG LABEL: Leflunomide
NDC: 68258-2992 | Form: TABLET
Manufacturer: Dispensing Solutions, Inc.
Category: prescription | Type: HUMAN PRESCRIPTION DRUG LABEL
Date: 20131017

ACTIVE INGREDIENTS: LEFLUNOMIDE 20 mg/1 1
INACTIVE INGREDIENTS: SILICON DIOXIDE; CROSCARMELLOSE SODIUM; LACTOSE MONOHYDRATE; MAGNESIUM STEARATE; STARCH, CORN; TALC

LEFLUNOMIDE TABLETS, USP 10 MG AND 20 MG
Rx only

CONTRAINDICATIONS AND WARNINGS

PREGNANCY

PREGNANCY MUST BE EXCLUDED BEFORE THE START OF TREATMENT WITH LEFLUNOMIDE TABLETS. LEFLUNOMIDE TABLETS ARE CONTRAINDICATED IN PREGNANT WOMEN, OR WOMEN OF CHILDBEARING POTENTIAL WHO ARE NOT USING RELIABLE CONTRACEPTION. (SEE CONTRAINDICATIONS AND WARNINGS.) PREGNANCY MUST BE AVOIDED DURING LEFLUNOMIDE TABLET TREATMENT OR PRIOR TO THE COMPLETION OF THE DRUG ELIMINATION PROCEDURE AFTER LEFLUNOMIDE TABLET TREATMENT.

HEPATOTOXICITY

SEVERE LIVER INJURY, INCLUDING FATAL LIVER FAILURE, HAS BEEN REPORTED IN SOME PATIENTS TREATED WITH LEFLUNOMIDE. PATIENTS WITH PRE-EXISTING ACUTE OR CHRONIC LIVER DISEASE, OR THOSE WITH SERUM ALANINE AMINOTRANSFERASE (ALT) >2XULN BEFORE INITIATING TREATMENT, SHOULD NOT BE TREATED WITH LEFLUNOMIDE. USE CAUTION WHEN LEFLUNOMIDE IS GIVEN WITH OTHER POTENTIALLY HEPATOTOXIC DRUGS.

MONITORING OF ALT LEVELS IS RECOMMENDED AT LEAST MONTHLY FOR SIX MONTHS AFTER STARTING LEFLUNOMIDE, AND THEREAFTER EVERY 6-8 WEEKS. IF ALT ELEVATION > 3 FOLD ULN OCCURS, INTERRUPT LEFLUNOMIDE THERAPY WHILE INVESTIGATING THE PROBABLE CAUSE OF THE ALT ELEVATION BY CLOSE OBSERVATION AND ADDITIONAL TESTS. IF LIKELY LEFLUNOMIDE-INDUCED, START CHOLESTYRAMINE WASHOUT AND MONITOR LIVER TESTS WEEKLY UNTIL NORMALIZED. IF LEFLUNOMIDE-INDUCED LIVER INJURY IS UNLIKELY BECAUSE SOME OTHER PROBABLE CAUSE HAS BEEN FOUND, RESUMPTION OF LEFLUNOMIDE THERAPY MAY BE CONSIDERED. (SEE WARNINGS – HEPATOTOXICITY).

DESCRIPTION

Leflunomide is a pyrimidine synthesis inhibitor. The chemical name for leflunomide is N-(4’-trifluoromethylphenyl)-5-methylisoxazole-4-carboxamide. It has a molecular formula C12H9F3N2O2, a molecular weight of 270.2 and the following structural formula:

Leflunomide is available for oral administration as tablets containing 10 or 20 mg of active drug. Combined with leflunomide are the following inactive ingredients: colloidal silicon dioxide, croscarmellose sodium, lactose monohydrate, magnesium stearate, pregelatinized starch, and talc.

CLINICAL PHARMACOLOGY

Mechanism of Action

Leflunomide is an isoxazole immunomodulatory agent which inhibits dihydroorotate dehydrogenase (an enzyme involved in de novo pyrimidine synthesis) and has antiproliferative activity. Several in vivo and in vitro experimental models have demonstrated an anti-inflammatory effect.

Pharmacokinetics

Following oral administration, leflunomide is metabolized to an active metabolite A77 1726 (hereafter referred to as M1) which is responsible for essentially all of its activity in vivo. Plasma levels of leflunomide are occasionally seen, at very low levels. Studies of the pharmacokinetics of leflunomide have primarily examined the plasma concentrations of this active metabolite.

Absorption

Following oral administration, peak levels of the active metabolite, M1, occurred between 6 - 12 hours after dosing. Due to the very long half-life of M1 (~2 weeks), a loading dose of 100 mg for 3 days was used in clinical studies to facilitate the rapid attainment of steady-state levels of M1. Without a loading dose, it is estimated that attainment of steady-state plasma concentrations would require nearly two months of dosing. The resulting plasma concentrations following both loading doses and continued clinical dosing indicate that M1 plasma levels are dose proportional.

Table 1. Pharmacokinetic Parameters for M1 after Administration of Leflunomide at Doses of 5, 10, and 25 mg/day for 24 Weeks to Patients (n=54) with Rheumatoid Arthritis (Mean ± SD) (Study YU204)
Maintenance (Loading) Dose
Parameter |  |  | 25 mg (100 mg)
C24 (Day 1) (mcg/mL)^1 | 4.0 ± 0.6 | 8.4 ± 2.1 | 8.5 ± 2.2
C24 (ss) (mcg/mL)^2 | 8.8 ± 2.9 | 18 ± 9.6 | 63 ± 36
t1/2(DAYS) | 15 ± 3 | 14 ± 5 | 18 ± 9
^1 Concentration at 24 hours after loading dose
^2 Concentration at 24 hours after maintenance doses at steady-state

Relative to an oral solution, leflunomide tablets are 80% bioavailable. Coadministration of leflunomide tablets with a high fat meal did not have a significant impact on M1 plasma levels.

Distribution

M1 has a low volume of distribution (Vss = 0.13 L/kg) and is extensively bound (>99.3%) to albumin in healthy subjects. Protein binding has been shown to be linear at therapeutic concentrations. The free fraction of M1 is slightly higher in patients with rheumatoid arthritis and approximately doubled in patients with chronic renal failure; the mechanism and significance of these increases are unknown.

Metabolism

Leflunomide is metabolized to one primary (M1) and many minor metabolites. Of these minor metabolites, only 4-trifluoromethylaniline (TFMA) is quantifiable, occurring at low levels in the plasma of some patients. The parent compound is rarely detectable in plasma. At the present time the specific site of leflunomide metabolism is unknown. In vivo and in vitro studies suggest a role for both the GI wall and the liver in drug metabolism. No specific enzyme has been identified as the primary route of metabolism for leflunomide; however, hepatic cytosolic and microsomal cellular fractions have been identified as sites of drug metabolism.

Elimination

The active metabolite M1 is eliminated by further metabolism and subsequent renal excretion as well as by direct biliary excretion. In a 28 day study of drug elimination (n=3) using a single dose of radiolabeled compound, approximately 43% of the total radioactivity was eliminated in the urine and 48% was eliminated in the feces. Subsequent analysis of the samples revealed the primary urinary metabolites to be leflunomide glucuronides and an oxanilic acid derivative of M1. The primary fecal metabolite was M1. Of these two routes of elimination, renal elimination is more significant over the first 96 hours after which fecal elimination begins to predominate. In a study involving the intravenous administration of M1, the clearance was estimated to be 31 mL/hr.

In small studies using activated charcoal (n=1) or cholestyramine (n=3) to facilitate drug elimination, the in vivo plasma half-life of M1 was reduced from >1 week to approximately 1 day. (See PRECAUTIONS ─ General - Need For Drug Elimination). Similar reductions in plasma half-life were observed for a series of volunteers (n=96) enrolled in pharmacokinetic trials who were given cholestyramine. This suggests that biliary recycling is a major contributor to the long elimination half-life of M1. Studies with both hemodialysis and CAPD (chronic ambulatory peritoneal dialysis) indicate that M1 is not dialyzable.

Special Populations

Gender. Gender has not been shown to cause a consistent change in the in vivo pharmacokinetics of M1.

Age. Age has been shown to cause a change in the in vivo pharmacokinetics of M1 (see CLINICAL PHARMACOLOGY – Special Populations - Pediatrics).

Smoking. A population based pharmacokinetic analysis of the phase Ill data indicates that smokers have a 38% increase in clearance over non-smokers; however, no difference in clinical efficacy was seen between smokers and nonsmokers.

Chronic Renal Insufficiency. In single dose studies in patients (n=6) with chronic renal insufficiency requiring either chronic ambulatory peritoneal dialysis (CAPD) or hemodialysis, neither had a significant impact on circulating levels of M1. The free fraction of M1 was almost doubled, but the mechanism of this increase is not known. In light of the fact that the kidney plays a role in drug elimination, and without adequate studies of leflunomide use in subjects with renal insufficiency, caution should be used when leflunomide is administered to these patients.

Hepatic Insufficiency. Studies of the effect of hepatic insufficiency on M1 pharmacokinetics have not been done. Given the need to metabolize leflunomide into the active species, the role of the liver in drug elimination/recycling, and the possible risk of increased hepatic toxicity, the use of leflunomide in patients with hepatic insufficiency is not recommended.

Pediatrics

The pharmacokinetics of M1 following oral administration of leflunomide have been investigated in 73 pediatric patients with polyarticular course Juvenile Rheumatoid Arthritis (JRA) who ranged in age from 3 to 17 years. The results of a population pharmacokinetic analysis of these trials have demonstrated that pediatric patients with body weights ≤40 kg have a reduced clearance of M1 (see Table 2) relative to adult rheumatoid arthritis patients.

Table 2: Population Pharmacokinetic Estimate of M1 Clearance Following Oral Administration of Leflunomide in Pediatric Patients with Polyarticular Course JRA Mean ±SD [Range]
N | Body Weight (kg) | CL (mL/h)
10 | <20 | 18 ± 9.8 [6.8-37]
30 | 20-40 | 18 ± 9.5 [4.2-43]
33 | >40 | 26 ± 16 [9.7-93.6]

Drug Interactions

In vivo drug interaction studies have demonstrated a lack of a significant drug interaction between leflunomide and tri-phasic oral contraceptives, and cimetidine.

In vitro studies of protein binding indicated that warfarin did not affect M1 protein binding. At the same time M1 was shown to cause increases ranging from 13 - 50% in the free fraction of diclofenac, ibuprofen and tolbutamide at concentrations in the clinical range. In vitro studies of drug metabolism indicate that M1 inhibits CYP 450 2C9, which is responsible for the metabolism of phenytoin, tolbutamide, warfarin and many NSAIDs. M1 has been shown to inhibit the formation of 4’-hydroxydiclofenac from diclofenac in vitro. The clinical significance of these findings with regard to phenytoin and tolbutamide is unknown; however, there was extensive concomitant use of NSAIDs in the clinical studies and no differential effect was observed. (See PRECAUTIONS – Drug Interactions.)

Methotrexate. Coadministration, in 30 patients, of leflunomide (100 mg/day x 2 days followed by 10 - 20 mg/day) with methotrexate (10 - 25 mg/week, with folate) demonstrated no pharmacokinetic interaction between the two drugs. However, coadministration increased risk of hepatotoxicity (see PRECAUTIONS – Drug Interactions - Hepatotoxic Drugs).

Rifampin. Following concomitant administration of a single dose of leflunomide to subjects receiving multiple doses of rifampin, M1 peak levels were increased (~40%) over those seen when leflunomide was given alone. Because of the potential for leflunomide levels to continue to increase with multiple dosing, caution should be used if patients are to receive both leflunomide and rifampin.

CLINICAL STUDIES

ADULTS

The efficacy of leflunomide in the treatment of rheumatoid arthritis (RA) was demonstrated in three controlled trials showing reduction in signs and symptoms and inhibition of structural damage.

1. Reduction of signs and symptoms
  Relief of signs and symptoms was assessed using the American College of Rheumatology (ACR)20 Responder Index, a composite of clinical, laboratory, and functional measures in rheumatoid arthritis. An “ACR20 Responder” is a patient who had >20% improvement in both tender and swollen joint counts and in 3 of the following 5 criteria: physician global assessment, patient global assessment, functional ability measure [Modified Health Assessment Questionnaire (MHAQ)], visual analog pain scale, and erythrocyte sedimentation rate or C-reactive protein. An “ACR20 Responder at Endpoint” is a patient who completed the study and was an ACR20 Responder at the completion of the study.
2. Inhibition of structural damage
  Inhibition of structural damage compared to control was assessed using the Sharp Score (Sharp, JT. Scoring Radiographic Abnormalities in Rheumatoid Arthritis, Radiologic Clinics of North America, 1996; vol. 34, pp. 233-241), a composite score of X-ray erosions and joint space narrowing in hands/wrists and forefeet.

Improvement in physical function

Improvement in physical function was assessed using the Health Assessment Questionnaire (HAQ) and the Medical Outcomes Survey Short Form (SF-36).

In all leflunomide monotherapy studies, an initial loading dose of 100 mg per day for three days only was used followed by 20 mg per day thereafter.

US301 Clinical Trial in Adults

Study US301, a 2 year study, randomized 482 patients with active RA of at least 6 months duration to leflunomide 20 mg/day (n=182), methotrexate 7.5 mg/week increasing to 15 mg/week (n=182), or placebo (n=118). All patients received folate 1 mg BID. Primary analysis was at 52 weeks with blinded treatment to 104 weeks.

Overall, 235 of the 508 randomized treated patients (482 in primary data analysis and an additional 26 patients), continued into a second 12 months of double-blind treatment (98 leflunomide, 101 methotrexate, 36 placebo). Leflunomide dose continued at 20 mg/day and the methotrexate dose could be increased to a maximum of 20 mg/week. In total, 190 patients (83 leflunomide, 80 methotrexate, 27 placebo) completed
2 years of double-blind treatment.

The rate and reason for withdrawal is summarized in Table 3.

Table 3: Withdrawals in US301
 | n(%) patients
 | Leflunomide |  | Methotrexate
 | 190 | 128 | 190
Withdrawals in Year-1
Lack of efficacy | 33 (17.4) | 70 (54.7) | 50 (26.3)
Safety | 44 (23.2) | 12 (9.4) | 22 (11.6)
Other^1 | 15 (7.9) | 10 (7.8) | 17 (9.0)
Total | 92 (48.4) | 92 (71.9) | 89 (46.8)
Patients entering Year 2 | 98 | 36 | 101
Withdrawals in Year-2
Lack of efficacy | 4 (4.1) | 1 (2.8) | 4 (4.0)
Safety | 8 (8.2) | 0 (0.0) | 10 (9.9)
Other^1 | 3 (3.1) | 8 (22.2) | 7 (6.9)
Total | 15 (15.3) | 9 (25.0) | 21 (20.8)
^1 Includes: lost to follow up, protocol violation, noncompliance, voluntary withdrawal, investigator discretion.

MN301/303/305 Clinical Trial in Adults

Study MN301 randomized 358 patients with active RA to leflunomide 20 mg/day (n=133), sulfasalazine 2.0 g/day (n=133), or placebo (n=92). Treatment duration was 24 weeks. An extension of the study was an optional 6-month blinded continuation of MN301 without the placebo arm, resulting in a 12-month comparison of leflunomide and sulfasalazine (study MN303).

Of the 168 patients who completed 12 months of treatment in MN301 and MN303, 146 patients (87%) entered a 1-year extension study of double blind active treatment (MN305; 60 leflunomide, 60 sulfasalazine, 26 placebo/sulfasalazine). Patients continued on the same daily dosage of leflunomide or sulfasalazine that they had been taking at the completion of MN301/303. A total of 121 patients (53 leflunomide, 47 sulfasalazine, 21 placebo/sulfasalazine) completed the 2 years of double blind treatment.

Patient withdrawal data in MN301/303/305 is summarized in Table 4.

Table 4: Withdrawals in study MN301/303/305
 | n(%) patients
 | Leflunomide | Placebo | Sulfasalazine
 | 133 | 92 | 133
Withdrawals in MN301 (Mo 0-6)
Lack of efficacy | 10 (7.5) | 29 (31.5) | 14 (10.5)
Safety | 19 (14.3) | 6 (6.5) | 25 (18.8)
Other^1 | 8 (6.0) | 6 (6.5) | 11 (8.3)
Total | 37 (27.8) | 41 (44.6) | 50 (37.6)
Patients entering MN303 | 80 |  | 76
Withdrawals in MN303 (Mo 7-12)
Lack of efficacy | 4 (5.0) |  | 2 (2.6)
Safety | 2 (2.5) |  | 5 (6.6)
Other^1 | 3 (3.8) |  | 1 (1.3)
Total | 9 (11.3) |  | 8 (10.5)
Patients entering MN305 | 60 |  | 60
Withdrawals in MN305 (Mo 13-24)
Lack of efficacy | 0 (0.0) |  | 3 (5.0)
Safety | 6 (10.0) |  | 8 (13.3)
Other^1 | 1 (1.7) |  | 2 (3.3)
Total | 7 (11.7) |  | 13 (21.7)
^1 Includes: lost to follow up, protocol violation, noncompliance, voluntary withdrawal, investigator discretion.

MN302/304 Clinical Trial in Adults

Study MN302 randomized 999 patients with active RA to leflunomide 20 mg/day (n=501) or methotrexate at 7.5 mg/week increasing to 15 mg/week (n=498). Folate supplementation was used in 10% of patients. Treatment duration was 52 weeks.

Of the 736 patients who completed 52 weeks of treatment in study MN302, 612 (83%) entered the double-blind, 1-year extension study MN304 (292 leflunomide, 320 methotrexate). Patients continued on the same daily dosage of leflunomide or methotrexate that they had been taking at the completion of MN302. There were 533 patients (256 leflunomide, 277 methotrexate) who completed 2 years of double-blind treatment. Patient withdrawal data in MN302/304 is summarized in Table 5.

Table 5: Withdrawals in MN302/304
 | n(%) patients
 | Leflunomide | Methotrexate
 | 501 | 498
Withdrawals in MN302 (Year-1)
Lack of efficacy | 37 (7.4) | 15 (3.0)
Safety | 98 (19.6) | 79 (15.9)
Other1 | 17 (3.4) | 17 (3.4)
Withdrawals in MN302 (Year-1)
Total | 152 (30.3) | 111 (22.3)
Patients entering MN304 | 292 | 320
Total | 152 (30.3) | 111 (22.3)
Patients entering MN304 | 292 | 320
Withdrawals in MN304 (Year-2)
Lack of efficacy | 13 (4.5) | 9 (2.8)
Safety | 11 (3.8) | 22 (6.9)
Other^1 | 12 (4.1) | 12 (3.8)
Total | 36 (12.3) | 43 (13.4)
^1 Includes: lost to follow up, protocol violation, noncompliance, voluntary withdrawal, investigator discretion

Clinical Trial Data

1. Signs and symptoms Rheumatoid Arthritis

The ACR20 Responder at Endpoint rates are shown in Figure 1. Leflunomide was statistically significantly superior to placebo in reducing the signs and symptoms of RA by the primary efficacy analysis, ACR20 Responder at Endpoint, in study US301 (at the primary 12 months endpoint) and MN301 (at 6 month endpoint).

ACR20 Responder at Endpoint rates with leflunomide treatment were consistent across the 6 and 12 month studies (41 - 49%). No consistent differences were demonstrated between leflunomide and methotrexate or between leflunomide and sulfasalazine. Leflunomide treatment effect was evident by 1 month, stabilized by 3 - 6 months, and continued throughout the course of treatment as shown in Figure 2.

Figure 1

 | Comparisons | 95% Confidence Interval | p Value
US301 | Leflunomide vs. Placebo | (12, 32) | <0.0001
 | Methotrexate vs. Placebo | (8, 30) | <0.0001
 | Leflunomide vs. Methotrexate | (-4, 16) | NS
MN301 | Leflunomide vs. Placebo | (7, 33) | 0.0026
 | Sulfasalazine vs. Placebo | (4, 29) | 0.0121
 | Leflunomide vs.Sulfasalazine | (-8, 16) | NS
MN302 | Leflunomide vs.Methotrexate | (-19, -7) | <0.0001

Figure 2

ACR50 and ACR70 Responders are defined in an analogous manner to the ACR20 Responder, but use improvements of 50% or 70%, respectively (Table 6). Mean change for the individual components of the ACR Responder Index are shown in Table 7.

Table 6. Summary of ACR Response Rates*
Study and Treatment Group | ACR20 | ACR50[ | ACR70
Placebo-Controlled Studies
US301 (12 months)
Leflunomide (n=178)† | 52.2‡ | 34.3‡ | 20.2‡
Placebo (n=118) † | 26.3 | 7.6 | 4.2
Methotrexate (n=180) † | 45.6 | 22.8 | 9.4
MN301 (6 months)
Leflunomide (n=130)† | 54.6‡ | 33.1‡ | 10.0§
Placebo (n=91) † | 28.6 | 14.3 | 2.2
Sulfasalazine (n=132) † | 56.8 | 30.3 | 7.6
Non-Placebo Active-Controlled Studies
MN302 (12 months)
Leflunomide (n=495)† | 51.1 | 31.1 | 9.9
Methotrexate (n=489) † | 65.2 | 43.8 | 16.4
* Intent to treat (ITT) analysis using last observation carried forward (LOCF) technique for patients who discontinued early.
† N is the number of ITT patients for whom adequate data were available to calculate the indicated rates.
‡ p<0.001 leflunomide vs placebo
§ p<0.02 leflunomide vs placebo

Table 7 shows the results of the components of the ACR Response criteria for US301, MN301, and MN302. Leflunomide was significantly superior to placebo in all components of the ACR Response criteria in study US301 and MN301. In addition, leflunomide was significantly superior to placebo in improving morning stiffness, a measure of RA disease activity, not included in the ACR Response criteria. No consistent differences were demonstrated between leflunomide and the active comparators.

Table 7. Mean Change in the Components of the ACR Responder Index*
Components | Placebo-Controlled Studies | Non-placebo Controlled Study
 | US301 (12 months) | MN301 Non-US (6 months) | MN302 Non-US (12 months)
 | Leflu-nomide | Metho-trexate | Placebo | Leflu-nomide | Sulfa-salazine | Placebo | Leflu-nomide | Metho-trexate
Tender joint count^1 | -7.7 | -6.6 | -3.0 | -9.7 | -8.1 | -4.3 | -8.3 | -9.7
Swollen joint count^1 | -5.7 | -5.4 | -2.9 | -7.2 | -6.2 | -3.4 | -6.8 | -9.0
Patient global assessment^2 | -2.1 | -1.5 | 0.1 | -2.8 | -2.6 | -0.9 | -2.3 | -3.0
Physician global assessment^2 | -2.8 | -2.4 | -1.0 | -2.7 | -2.5 | -0.8 | -2.3 | -3.1
Physical function/disability (MHAQ/HAQ) | -0.29 | -0.15 | 0.07 | -0.50 | -0.29 | -0.04 | -0.37 | -0.44
Pain intensity^2 | -2.2 | -1.7 | -0.5 | -2.7 | -2.0 | -0.9 | -2.1 | -2.9
Erythrocyte Sedimentation rate | -6.26 | -6.48 | 2.56 | -7.48 | -16.56 | 3.44 | -10.12 | -22.18
C-reactive protein | -0.62 | -0.50 | 0.47 | -2.26 | -1.19 | 0.16 | -1.86 | -2.45
Not included in the ACR Responder Index
Morning Stiffness (min) | -101.4 | -88.7 | 14.7 | -93.0 | -42.4 | -6.8 | -63.7 | -86.6
* Last Observation Carried Forward; Negative Change Indicates Improvement
^1 Based on 28 joint count
^2 Visual Analog Scale – 0=Best; 10=Worst

2. Maintenance of effect

After completing 12 months of treatment, patients continuing on study treatment were evaluated for an additional 12 months of double-blind treatment (total treatment period of 2 years) in studies US301, MN305, and MN304. ACR Responder rates at 12 months were maintained over 2 years in most patients continuing a second year of treatment.

Improvement from baseline in the individual components of the ACR Responder criteria was also sustained in most patients during the second year of leflunomide treatment in all three trials.

3. Inhibition of structural damage

The change from baseline to endpoint in progression of structural disease, as measured by the Sharp X-ray score, is displayed in Figure 3. Leflunomide was statistically significantly superior to placebo in inhibiting the progression of disease by the Sharp Score. No consistent differences were demonstrated between leflunomide and methotrexate or between leflunomide and sulfasalazine.

Figure 3

 | Comparisons | 95% Confidence Interval | p Value
US301 | Leflunomide vs. Placebo | (-4.0, -1.1) | 0.0007
 | Methotrexate vs. Placebo | (-2.6, -0.2) | 0.0196
 | Leflunomide vs. Methotrexate | (-2.3, 0.0) | 0.0499
MN301 | Leflunomide vs. Placebo | (-6.2, -1.8) | 0.0004
 | Sulfasalazine vs. Placebo | (-6.9, 0.0) | 0.0484
 | Leflunomide vs. Sulfasalazine | (-3.3, 1.2) | NS
MN302 | Leflunomide vs.Methotrexate | (-2.2, 7.4) | NS

4. Improvement of physical function

The Health Assessment Questionnaire (HAQ) assesses a patient's physical function and degree of disability. The mean change from baseline in functional ability as measured by the HAQ Disability Index (HAQ DI) in the 6 and 12 month placebo and active controlled trials is shown in Figure 4. Leflunomide was statistically significantly superior to placebo in improving physical function. Superiority to placebo was demonstrated consistently across all eight HAQ DI subscales (dressing, arising, eating, walking, hygiene, reach, grip and activities) in both placebo controlled studies.

The Medical Outcomes Survey Short Form 36 (SF-36), a generic health-related quality of life questionnaire, further addresses physical function. In US301, at 12 months, Leflunomide provided statistically significant improvements compared to placebo in the Physical Component Summary (PCS) Score.

Figure 4

 | Comparisons | 95% Confidence Interval | p Value
US301 | Leflunomide vs. Placebo | (-0.58, -0.29) | 0.0001
 | Leflunomide vs. Methotrexate | (-0.34, -0.07) | 0.0026
MN301 | Leflunomide vs. Placebo | (-0.67, -0.36) | < 0.0001
 | Leflunomide vs.Sulfasalazine | (-0.33, -0.03) | 0.0163
MN302 | Leflunomide vs.Methotrexate | (0.01, 0.16) | 0.0221
US301 | Leflunomide vs. Placebo | (-0.58, -0.29) | 0.0001
US301 | Leflunomide vs. Placebo | (-0.58, -0.29) | 0.0001

Maintenance of effect

The improvement in physical function demonstrated at 6 and 12 months was maintained over two years. In those patients continuing therapy for a second year, this improvement in physical function as measured by HAQ and SF-36 (PCS) was maintained.

PEDIATRICS

Clinical Trials in Pediatrics

Leflunomide was studied in a single multicenter, double-blind, active-controlled trial in 94 patients (1:1 randomization) with polyarticular course juvenile rheumatoid arthritis (JRA) as defined by the American College of Rheumatology (ACR). Approximately 68% of pediatric patients receiving leflunomide, versus 89% of pediatric patients receiving the active comparator, improved by Week 16 (end-of-study) employing the JRA Definition of Improvement (DOI) ≥ 30 % responder endpoint. In this trial, the loading dose and maintenance dose of leflunomide was based on three weight categories: <20 kg, 20-40kg, and >40 kg. The response rate to leflunomide in pediatric patients ≤40 kg was less robust than in pediatric patients >40 kg suggesting suboptimal dosing in smaller weight pediatric patients, as studied, resulting in less than efficacious plasma concentrations, despite reduced clearance of M1. (See Pharmacokinetics - Pediatrics).

INDICATIONS AND USAGE

Leflunomide tablets are indicated in adults for the treatment of active rheumatoid arthritis (RA):

1. to reduce signs and symptoms
2. to inhibit structural damage as evidenced by X-ray erosions and joint space narrowing
3. to improve physical function

(see CLINICAL STUDIES).

Aspirin, nonsteroidal anti-inflammatory agents and/or low dose corticosteroids may be continued during treatment with leflunomide tablets (see PRECAUTIONS - Drug Interactions – NSAIDs). The combined use of leflunomide tablets with antimalarials, intramuscular or oral gold, D penicillamine, azathioprine, or methotrexate has not been adequately studied. (See WARNINGS - Immunosuppression Potential/Bone Marrow Suppression).

CONTRAINDICATIONS

Leflunomide tablets are contraindicated in patients with known hypersensitivity to leflunomide or any of the other components of leflunomide tablets.

Leflunomide tablets can cause fetal harm when administered to a pregnant woman. Leflunomide, when administered orally to rats during organogenesis at a dose of 15 mg/kg, was teratogenic (most notably anophthalmia or microophthalmia and internal hydrocephalus). The systemic exposure of rats at this dose was approximately 1/10 the human exposure level based on AUC. Under these exposure conditions, leflunomide also caused a decrease in the maternal body weight and an increase in embryolethality with a decrease in fetal body weight for surviving fetuses. In rabbits, oral treatment with 10 mg/kg of leflunomide during organogenesis resulted in fused, dysplastic sternebrae. The exposure level at this dose was essentially equivalent to the maximum human exposure level based on AUC. At a 1 mg/kg dose, leflunomide was not teratogenic in rats and rabbits.

When female rats were treated with 1.25 mg/kg of leflunomide beginning 14 days before mating and continuing until the end of lactation, the offspring exhibited marked (greater than 90%) decreases in postnatal survival. The systemic exposure level at 1.25 mg/kg was approximately 1/100 the human exposure level based on AUC.

Leflunomide tablets are contraindicated in women who are or may become pregnant. If this drug is used during pregnancy, or if the patient becomes pregnant while taking this drug, the patient should be apprised of the potential hazard to the fetus.

WARNINGS

Hepatotoxicity

Severe liver injury, including fatal liver failure, has been reported in some patients treated with leflunomide. Patients with pre-existing acute or chronic liver disease, or those with serum alanine aminotransferase (ALT) >2xULN before initiating treatment, should not be treated with leflunomide. Use caution when leflunomide is given with other potentially hepatotoxic drugs. Monitoring of ALT levels is recommended at least monthly for six months after starting leflunomide and thereafter every 6-8 weeks. If ALT elevation > 3 fold ULN occurs, interrupt leflunomide therapy while investigating the probable cause of the ALT elevation by close observation and additional tests. If likely leflunomide-induced, start cholestyramine washout and monitor liver tests weekly until normalized (see PRECAUTIONS - General - Need for Drug Elimination). If leflunomide-induced liver injury is unlikely because some other probable cause has been found, resumption of leflunomide therapy may be considered.

In addition, if leflunomide and methotrexate are given concomitantly, ACR guidelines for monitoring methotrexate liver toxicity must be followed with ALT, AST, and serum albumin testing monthly.

In clinical trials, leflunomide treatment as monotherapy or in combination with methotrexate was associated with elevations of liver enzymes, primarily ALT and AST, in a significant number of patients; these effects were generally reversible. Most transaminase elevations were mild (<2-fold ULN) and usually resolved while continuing treatment. Marked elevations (>3-fold ULN) occurred infrequently and reversed with dose reduction or discontinuation of treatment. Table 8 shows liver enzyme elevations seen with monthly monitoring in clinical trials US301 and MN301. It was notable that the absence of folate use in MN302 was associated with a considerably greater incidence of liver enzyme elevation on methotrexate.

Table 8. Liver Enzyme Elevations >3-fold Upper Limits of Normal (ULN)
 | US301 |  |  | MN301 |  |  | MN302*
 | LEF | PL | MTX | LEF | PL | SSZ | LEF | MTX
ALT (SGPT) >3-fold ULN | 8 | 3 | 5 | 2 | 1 | 2 | 13 | 83
(n %) | (4.4) | (2.5) | (2.7) | (1.5) | (1.1) | (1.5) | (2.6) | (16.7)
Reversed to <2-fold ULN: | 8 | 3 | 5 | 2 | 1 | 2 | 12 | 82
Timing of Elevation
0-3 Months | 6 | 1 | 1 | 2 | 1 | 2 | 7 | 27
4-6 Months | 1 | 1 | 3 | - | - | - | 1 | 34
7-9 Months | 1 | 1 | 1 | - | - | - | - | 16
10-12 Months | - | - | - | - | - | - | 5 | 6
* Only 10% of patients in MN302 received folate. All patients in US301 received folate.

In a 6 month study of 263 patients with persistent active rheumatoid arthritis despite methotrexate therapy, and with normal LFTs, leflunomide was added to a group of 130 patients starting at 10 mg per day and increased to 20 mg as needed. An increase in ALT greater than or equal to three times the ULN was observed in 3.8% of patients compared to 0.8% in 133 patients continued on methotrexate with placebo added.

Immunosuppression Potential/Bone Marrow Suppression

Leflunomide is not recommended for patients with severe immunodeficiency, bone marrow dysplasia, or severe, uncontrolled infections. In the event that a serious infection occurs, it may be necessary to interrupt therapy with leflunomide and administer cholestyramine or charcoal (see PRECAUTIONS - General - Need for Drug Elimination). Medications like leflunomide that have immunosuppression potential may cause patients to be more susceptible to infections, including opportunistic infections, especially Pneumocystis jiroveci pneumonia, tuberculosis (including extra-pulmonary tuberculosis), and aspergillosis. Severe infections including sepsis, which may be fatal, have been reported in patients receiving leflunomide, especially Pneumocystis jiroveci pneumonia and aspergillosis. Most of the reports were confounded by concomitant immunosuppressant therapy and/or comorbid illness which, in addition to rheumatoid disease, may predispose patients to infection.

There have been rare reports of pancytopenia, agranulocytosis and thrombocytopenia in patients receiving leflunomide alone. These events have been reported most frequently in patients who received concomitant treatment with methotrexate or other immunosuppressive agents, or who had recently discontinued these therapies; in some cases, patients had a prior history of a significant hematologic abnormality.

Patients taking leflunomide should have platelet, white blood cell count and hemoglobin or hematocrit monitored at baseline and monthly for six months following initiation of therapy and every 6- to 8 weeks thereafter. If used with concomitant methotrexate and/or other potential immunosuppressive agents, chronic monitoring should be monthly. If evidence of bone marrow suppression occurs in a patient taking leflunomide, treatment with leflunomide should be stopped, and cholestyramine or charcoal should be used to reduce the plasma concentration of leflunomide active metabolite (see PRECAUTIONS - General - Need for Drug Elimination).

In any situation in which the decision is made to switch from leflunomide to another anti-rheumatic agent with a known potential for hematologic suppression, it would be prudent to monitor for hematologic toxicity, because there will be overlap of systemic exposure to both compounds. Leflunomide washout with cholestyramine or charcoal may decrease this risk, but also may induce disease worsening if the patient had been responding to leflunomide treatment.

Skin Reactions

Rare cases of Stevens-Johnson syndrome and toxic epidermal necrolysis have been reported in patients receiving leflunomide. If a patient taking leflunomide develops any of these conditions, leflunomide therapy should be stopped, and a drug elimination procedure is recommended. (See PRECAUTIONS – General – Need for Drug Elimination).

Malignancy

The risk of malignancy, particularly lymphoproliferative disorders, is increased with the use of some immunosuppression medications. There is a potential for immunosuppression with leflunomide. No apparent increase in the incidence of malignancies and lymphoproliferative disorders was reported in the clinical trials of leflunomide, but larger and longer-term studies would be needed to determine whether there is an increased risk of malignancy or lymphoproliferative disorders with leflunomide.

Use in Women of Childbearing Potential

There are no adequate and well-controlled studies evaluating leflunomide in pregnant women. However, based on animal studies, leflunomide may increase the risk of fetal death or teratogenic effects when administered to a pregnant woman (see CONTRAINDICATIONS). Women of childbearing potential must not be started on leflunomide until pregnancy is excluded and it has been confirmed that they are using reliable contraception. Before starting treatment with leflunomide, patients must be fully counseled on the potential for serious risk to the fetus.

The patient must be advised that if there is any delay in onset of menses or any other reason to suspect pregnancy, they must notify the physician immediately for pregnancy testing and, if positive, the physician and patient must discuss the risk to the pregnancy. It is possible that rapidly lowering the blood level of the active metabolite by instituting the drug elimination procedure described below at the first delay of menses may decrease the risk to the fetus from leflunomide.

Upon discontinuing leflunomide, it is recommended that all women of childbearing potential undergo the drug elimination procedure described below. Women receiving leflunomide treatment who wish to become pregnant must discontinue leflunomide and undergo the drug elimination procedure described below which includes verification of M1 metabolite plasma levels less than 0.02 mg/L (0.02 µg/mL). Human plasma levels of the active metabolite (M1) less than 0.02 mg/L (0.02 µg/mL) are expected to have minimal risk based on available animal data.

Drug Elimination Procedure

The following drug elimination procedure is recommended to achieve non-detectable plasma levels (less than 0.02 mg/L or 0.02 µg/mL) after stopping treatment with leflunomide:

1. Administer cholestyramine 8 grams 3 times daily for 11 days. (The 11 days do not need to be consecutive unless there is a need to lower the plasma level rapidly.)
2. Verify plasma levels less than 0.02 mg/L (0.02 µg/mL) by two separate tests at least 14 days apart. If plasma levels are higher than 0.02 mg/L, additional cholestyramine treatment should be considered.

Without the drug elimination procedure, it may take up to 2 years to reach plasma M1 metabolite levels less than 0.02 mg/L due to individual variation in drug clearance.

PRECAUTIONS

General

Need for Drug Elimination

The active metabolite of leflunomide is eliminated slowly from the plasma. In instances of any serious toxicity from leflunomide, including hypersensitivity, use of a drug elimination procedure as described in this section is highly recommended to reduce the drug concentration more rapidly after stopping leflunomide therapy. If hypersensitivity is the suspected clinical mechanism, more prolonged cholestyramine or charcoal administration may be necessary to achieve rapid and sufficient clearance. The duration may be modified based on the clinical status of the patient.

Cholestyramine given orally at a dose of 8 g three times a day for 24 hours to three healthy volunteers decreased plasma levels of M1 by approximately 40% in 24 hours and by 49 to 65% in 48 hours.

Administration of activated charcoal (powder made into a suspension) orally or via nasogastric tube (50 g every 6 hours for 24 hours) has been shown to reduce plasma concentrations of the active metabolite, M1, by 37% in 24 hours and by 48% in 48 hours.

These drug elimination procedures may be repeated if clinically necessary.

Respiratory

Interstitial lung disease has been reported during treatment with leflunomide and has been associated with fatal outcomes (see ADVERSE REACTIONS). Interstitial lung disease is a potentially fatal disorder, which may occur acutely at any time during therapy and has a variable clinical presentation. New onset or worsening pulmonary symptoms, such as cough and dyspnea, with or without associated fever, may be a reason for discontinuation of the therapy and for further investigation, as appropriate. If discontinuation of the drug is necessary, initiation of wash-out procedures should be considered. (See WARNINGS - Drug Elimination Procedure).

Tuberculosis Reactivation

Prior to initiating immunomodulatory therapies, including leflunomide, patients should be screened for latent tuberculosis infection with a tuberculin skin test. leflunomide has not been studied in patients with a positive tuberculosis screen, and the safety of leflunomide in individuals with latent tuberculosis infection is unknown. Patients testing positive in tuberculosis screening should be treated by standard medical practice prior to therapy with leflunomide.

Renal Insufficiency

Single dose studies in dialysis patients show a doubling of the free fraction of M1 in plasma. There is no clinical experience in the use of leflunomide in patients with renal impairment. Caution should be used when administering this drug in this population.

Vaccinations

No clinical data are available on the efficacy and safety of vaccinations during leflunomide treatment. Vaccination with live vaccines is, however, not recommended. The long half-life of leflunomide should be considered when contemplating administration of a live vaccine after stopping leflunomide.

Blood Pressure Monitoring

Blood pressure should be checked before start of leflunomide treatment and periodically thereafter.

Information for Patients

- The potential for increased risk of birth defects should be discussed with female patients of childbearing potential. It is recommended that physicians advise women that they may be at increased risk of having a child with birth defects if they are pregnant when taking leflunomide, become pregnant while taking leflunomide, or do not wait to become pregnant until they have stopped taking leflunomide and followed the drug elimination procedure (as described in WARNINGS - Use In Women of Childbearing Potential - Drug Elimination Procedure).
- Patients should be advised of the possibility of rare, serious skin reactions. Patients should be instructed to inform their physicians promptly if they develop a skin rash or mucous membrane lesions.
- Patients should be advised of the potential hepatotoxic effects of leflunomide and of the need for monitoring liver enzymes. Patients should be instructed to notify their physicians if they develop symptoms such as unusual tiredness, abdominal pain or jaundice.
- Patients should be advised that they may develop a lowering of their blood counts and should have frequent hematologic monitoring. This is particularly important for patients who are receiving other immunosuppressive therapy concurrently with leflunomide, who have recently discontinued such therapy before starting treatment with leflunomide, or who have had a history of a significant hematologic abnormality. Patients should be instructed to notify their physicians promptly if they notice symptoms of pancytopenia (such as easy bruising or bleeding, recurrent infections, fever, paleness or unusual tiredness).
- Patients should be informed about the early warning signs of interstitial lung disease and asked to contact their physician as soon as possible if these symptoms appear or worsen during therapy.

Laboratory Tests

Hematologic Monitoring

At minimum, patients taking leflunomide should have platelet, white blood cell count and hemoglobin or hematocrit monitored at baseline and monthly for six months following initiation of therapy and every 6 to 8 weeks thereafter.

Bone Marrow Suppression Monitoring

If used concomitantly with immunosuppressants such as methotrexate, chronic monitoring should be monthly. (See WARNINGS - Immunosuppression Potential/Bone Marrow Suppression).

Liver Enzyme Monitoring

At minimum, ALT (SGPT) must be performed at baseline and at least monthly for six months after starting leflunomide, and thereafter every 6 to 8 weeks. In addition, if leflunomide and methotrexate are given concomitantly, ACR guidelines for monitoring methotrexate liver toxicity must be followed with ALT, AST, and serum albumin testing every month. (See WARNINGS - Hepatotoxicity.)

Due to a specific effect on the brush border of the renal proximal tubule, leflunomide has a uricosuric effect. A separate effect of hypophosphaturia is seen in some patients. These effects have not been seen together, nor have there been alterations in renal function.

Drug Interactions

Cholestyramine and Charcoal

Administration of cholestyramine or activated charcoal in patients (n=13) and volunteers (n=96) resulted in a rapid and significant decrease in plasma M1 (the active metabolite of leflunomide) concentration (see PRECAUTIONS - General - Need for Drug Elimination).

Hepatotoxic Drugs

Increased side effects may occur when leflunomide is given concomitantly with hepatotoxic substances. This is also to be considered when leflunomide treatment is followed by such drugs without a drug elimination procedure. In a small (n=30) combination study of leflunomide with methotrexate, a 2- to 3-fold elevation in liver enzymes was seen in 5 of 30 patients. All elevations resolved, 2 with continuation of both drugs and 3 after discontinuation of leflunomide. A >3-fold increase was seen in another 5 patients. All of these also resolved, 2 with continuation of both drugs and 3 after discontinuation of leflunomide. Three patients met “ACR criteria” for liver biopsy (1: Roegnik Grade I, 2: Roegnik Grade llla). No pharmacokinetic interaction was identified (see CLINICAL PHARMACOLOGY).

NSAIDs

In in vitro studies, M1 was shown to cause increases ranging from 13 - 50% in the free fraction of diclofenac and ibuprofen at concentrations in the clinical range. The clinical significance of this finding is unknown; however, there was extensive concomitant use of NSAIDs in clinical studies and no differential effect was observed.

Tolbutamide

In in vitro studies, M1 was shown to cause increases ranging from 13 - 50% in the free fraction of tolbutamide at concentrations in the clinical range. The clinical significance of this finding is unknown.

Rifampin

Following concomitant administration of a single dose of leflunomide to subjects receiving multiple doses of rifampin, M1 peak levels were increased (~40%) over those seen when leflunomide was given alone. Because of the potential for leflunomide levels to continue to increase with multiple dosing, caution should be used if patients are to be receiving both leflunomide and rifampin.

Warfarin

Increased INR (International Normalized Ratio) when leflunomide and warfarin were co-administered has been rarely reported.

Carcinogenesis, Mutagenesis, and Impairment of Fertility

No evidence of carcinogenicity was observed in a 2-year bioassay in rats at oral doses of leflunomide up to the maximally tolerated dose of 6 mg/kg (approximately 1/40 the maximum human M1 systemic exposure based on AUC). However, male mice in a 2-year bioassay exhibited an increased incidence in lymphoma at an oral dose of 15 mg/kg, the highest dose studied (1.7 times the human M1 exposure based on AUC). Female mice, in the same study, exhibited a dose-related increased incidence of bronchoalveolar adenomas and carcinomas combined beginning at 1.5 mg/kg (approximately 1/10 the human M1 exposure based on AUC). The significance of the findings in mice relative to the clinical use of leflunomide is not known.

Leflunomide was not mutagenic in the Ames Assay, the Unscheduled DNA Synthesis Assay, or in the HGPRT Gene Mutation Assay. In addition, leflunomide was not clastogenic in the in vivo Mouse Micronucleus Assay nor in the in vivo Cytogenetic Test in Chinese Hamster Bone Marrow Cells. However, 4-trifluoromethylaniline (TFMA), a minor metabolite of leflunomide, was mutagenic in the Ames Assay and in the HGPRT Gene Mutation Assay, and was clastogenic in the in vitro Assay for Chromosome Aberrations in the Chinese Hamster Cells. TFMA was not clastogenic in the in vivo Mouse Micronucleus Assay nor in the in vivo Cytogenetic Test in Chinese Hamster Bone Marrow Cells. Leflunomide had no effect on fertility in either male or female rats at oral doses up to 4.0 mg/kg (approximately 1/30 the human M1 exposure based on AUC).

Pregnancy

Pregnancy Category X (see CONTRAINDICATIONS section). Pregnancy Registry: To monitor fetal outcomes of pregnant women exposed to leflunomide, health care providers are encouraged to register such patients by calling 1-877-311-8972.

Nursing Mothers

Leflunomide should not be used by nursing mothers. It is not known whether leflunomide is excreted in human milk. Many drugs are excreted in human milk, and there is a potential for serious adverse reactions in nursing infants from leflunomide. Therefore, a decision should be made whether to proceed with nursing or to initiate treatment with leflunomide, taking into account the importance of the drug to the mother.

Use in Males

Available information does not suggest that leflunomide would be associated with an increased risk of male-mediated fetal toxicity. However, animal studies to evaluate this specific risk have not been conducted. To minimize any possible risk, men wishing to father a child should consider discontinuing use of leflunomide and taking cholestyramine 8 grams 3 times daily for 11 days.

Pediatric Use

The safety and effectiveness of leflunomide in pediatric patients with polyarticular course juvenile rheumatoid arthritis (JRA) have not been fully evaluated. (See CLINICAL STUDIES and ADVERSE REACTIONS).

Geriatric Use

Of the total number of subjects in controlled clinical (Phase III) studies of leflunomide, 234 subjects were 65 years and over. No overall differences in safety or effectiveness were observed between these subjects and younger subjects, and other reported clinical experience has not identified differences in responses between the elderly and younger patients, but greater sensitivity of some older individuals cannot be ruled out. No dosage adjustment is needed in patients over 65.

ADVERSE REACTIONS

Adverse reactions associated with the use of leflunomide in RA include diarrhea, elevated liver enzymes (ALT and AST), alopecia and rash. In the controlled studies at one year, the following adverse events were reported, regardless of causality. (See Table 9.)

Table 9. Percentage Of Patients With Adverse Events ≥3% In Any Leflunomide Treated Group
 | All RA Studies | Placebo-Controlled Trials |  |  |  | Active-Controlled Trials
 |  | MN 301 and US 301 |  |  |  | MN 302*
 | LEF (N=1339)^1 | LEF (N=315) | PBO (N=210) | SSZ (N=133) | MTX (N=182) | LEF (N=501) | MTX (N=498)
BODY AS A WHOLE
Allergic Reaction | 2% | 5% | 2% | 0% | 6% | 1% | 2%
Asthenia | 3% | 6% | 4% | 5% | 6% | 3% | 3%
Flu Syndrome | 2% | 4% | 2% | 0% | 7% | 0% | 0%
Infection, upper respiratory | 4% | 0% | 0% | 0% | 0% | 0% | 0%
Injury Accident | 5% | 7% | 5% | 3% | 11% | 6% | 7%
Pain | 2% | 4% | 2% | 2% | 5% | 1% | <1%
Abdominal Pain | 6% | 5% | 4% | 4% | 8% | 6% | 4%
Back Pain | 5% | 6% | 3% | 4% | 9% | 8% | 7%
CARDIOVASCULAR
Hypertension^2 | 10% | 9% | 4% | 4% | 3% | 10% | 4%
New onset of hypertension |  | 1% | <1% | 0% | 2% | 2% | <1%
Chest Pain | 2% | 4% | 2% | 2% | 4% | 1% | 2%
GASTROINTESTINAL
Anorexia | 3% | 3% | 2% | 5% | 2% | 3% | 3%
Diarrhea | 17% | 27% | 12% | 10% | 20% | 22% | 10%
Dyspepsia | 5% | 10% | 10% | 9% | 13% | 6% | 7%
Gastroenteritis | 3% | 1% | 1% | 0% | 6% | 3% | 3%
Abnormal Liver Enzymes | 5% | 10% | 2% | 4% | 10% | 6% | 17%
Nausea | 9% | 13% | 11% | 19% | 18% | 13% | 18%
Gl/Abdominal Pain | 5% | 6% | 4% | 7% | 8% | 8% | 8%
Mouth Ulcer | 3% | 5% | 4% | 3% | 10% | 3% | 6%
Vomiting | 3% | 5% | 4% | 4% | 3% | 3% | 3%
METABOLIC AND NUTRITIONAL
Hypokalemia | 1% | 3% | 1% | 1% | 1% | 1% | <1%
Weight Loss^3 | 4% | 2% | 1% | 2% | 0% | 2% | 2%
MUSCULO-SKELETAL SYSTEM
Arthralgia | 1% | 4% | 3% | 0% | 9% | <1% | 1%
Leg Cramps | 1% | 4% | 2% | 2% | 6% | 0% | 0%
Joint Disorder | 4% | 2% | 2% | 2% | 2% | 8% | 6%
Synovitis | 2% | <1% | 1% | 0% | 2% | 4% | 2%
Tenosynovitis | 3% | 2% | 0% | 1% | 2% | 5% | 1%
NERVOUS SYSTEM
Dizziness | 4% | 5% | 3% | 6% | 5% | 7% | 6%
Headache | 7% | 13% | 11% | 12% | 21% | 10% | 8%
Paresthesia | 2% | 3% | 1% | 1% | 2% | 4% | 3%
RESPIRATORY SYSTEM
Bronchitis | 7% | 5% | 2% | 4% | 7% | 8% | 7%
Increased Cough | 3% | 4% | 5% | 3% | 6% | 5% | 7%
Respiratory Infection | 15% | 21% | 21% | 20% | 32% | 27% | 25%
Pharyngitis | 3% | 2% | 1% | 2% | 1% | 3% | 3%
Pneumonia | 2% | 3% | 0% | 0% | 1% | 2% | 2%
Rhinitis | 2% | 5% | 2% | 4% | 3% | 2% | 2%
Sinusitis | 2% | 5% | 5% | 0% | 10% | 1% | 1%
SKIN AND APPENDAGES
Alopecia | 10% | 9% | 1% | 6% | 6% | 17% | 10%
Eczema | 2% | 1% | 1% | 1% | 1% | 3% | 2%
Pruritus | 4% | 5% | 2% | 3% | 2% | 6% | 2%
Rash | 10% | 12% | 7% | 11% | 9% | 11% | 10%
Dry Skin | 2% | 3% | 2% | 2% | 0% | 3% | 1%
UROGENITAL SYSTEM
Urinary Tract Infection | 5% | 5% | 7% | 4% | 2% | 5% | 6%
* Only 10% of patients in MN302 received folate. All patients in US301 received folate; none in MN301 received folate.
^1 Includes all controlled and uncontrolled trials with leflunomide (duration up to 12 months).
^2 Hypertension as a preexisting condition was overrepresented in all leflunomide treatment groups in phase III trials.
^3 In a meta-analysis of all phase II and III studies, during the first 6 months in patients receiving leflunomide, 10% lost 10-19 lbs (24 cases per 100 patient years) and 2% lost at least 20 lbs (4 cases/100 patient years). Of patients receiving leflunomide, 4% lost 10% of their baseline weight during the first 6 months of treatment.

Adverse events during a second year of treatment with leflunomide in clinical trials were consistent with those observed during the first year of treatment and occurred at a similar or lower incidence.

In addition, the following adverse events have been reported in 1% to <3% of the RA patients in the leflunomide treatment group in controlled clinical trials.

Body as a Whole: abscess, cyst, fever, hernia, malaise, pain, neck pain, pelvic pain;

Cardiovascular: angina pectoris, migraine, palpitation, tachycardia, varicose vein, vasculitis, vasodilatation;

Gastrointestinal: cholelithiasis, colitis, constipation, esophagitis, flatulence, gastritis, gingivitis, melena, oral moniliasis, pharyngitis, salivary gland enlarged, stomatitis (or aphthous stomatitis), tooth disorder;

Endocrine: diabetes mellitus, hyperthyroidism;

Hemic and Lymphatic System: anemia (including iron deficiency anemia), ecchymosis;

Metabolic and Nutritional: creatine phosphokinase increased, hyperglycemia, hyperlipidemia, peripheral edema;

Musculo-Skeletal System: arthrosis, bone necrosis, bone pain, bursitis, muscle cramps, myalgia, tendon rupture;

Nervous System: anxiety, depression, dry mouth, insomnia, neuralgia, neuritis, sleep disorder, sweating increased, vertigo;

Respiratory System: asthma, dyspnea, epistaxis, lung disorder;

Skin and Appendages: acne, contact dermatitis, fungal dermatitis, hair discoloration, hematoma, herpes simplex, herpes zoster, maculopapular rash, nail disorder, skin discoloration, skin disorder, skin nodule, subcutaneous nodule, ulcer skin;

Special Senses: blurred vision, cataract, conjunctivitis, eye disorder, taste perversion;

Urogenital System: albuminuria, cystitis, dysuria, hematuria, menstrual disorder, prostate disorder, urinary frequency, vaginal moniliasis.

Other less common adverse events seen in clinical trials include: 1 case of anaphylactic reaction occurred in Phase 2 following rechallenge of drug after withdrawal due to rash (rare); urticaria; eosinophilia; transient thrombocytopenia (rare); and leukopenia <2000 WBC/mm^3 (rare).

Adverse events during a second year of treatment with leflunomide in clinical trials were consistent with those observed during the first year of treatment and occurred at a similar or lower incidence.

In post-marketing experience, the following have been reported rarely:

Body as a Whole: opportunistic infections, severe infections including sepsis that may be fatal;

Gastrointestinal: pancreatitis;

Hematologic: agranulocytosis, leukopenia, neutropenia, pancytopenia, thrombocytopenia;

Hypersensitivity: angioedema;

Hepatic: hepatitis, jaundice/cholestasis, severe liver injury such as hepatic failure and acute hepatic necrosis that may be fatal;

Respiratory: interstitial lung disease, including interstitial pneumonitis and pulmonary fibrosis, which may be fatal;

Nervous System: peripheral neuropathy;

Skin and Appendages: erythema multiforme, Stevens-Johnson syndrome, toxic epidermal necrolysis, vasculitis including cutaneous necrotizing vasculitis.

Adverse Reactions (Pediatric Patients)

The safety of leflunomide was studied in 74 patients with polyarticular course juvenile rheumatoid arthritis ranging in age from 3-17 years (47 patients from the active-controlled study and 27 from an open-label safety and pharmacokinetic study). The most common adverse events included abdominal pain, diarrhea, nausea, vomiting, oral ulcers, upper respiratory tract infections, alopecia, rash, headache, and dizziness. Less common adverse events included anemia, hypertension, and weight loss. Fourteen pediatric patients experienced ALT and/or AST elevations, nine between 1.2 and 3-fold the upper limit of normal, five between 3 and 8-fold the upper limit of normal.

DRUG ABUSE AND DEPENDENCE

Leflunomide has no known potential for abuse or dependence.

OVERDOSAGE

In mouse and rat acute toxicology studies, the minimally toxic dose for oral leflunomide was 200 - 500 mg/kg and 100 mg/kg, respectively (approximately >350 times the maximum recommended human dose, respectively).

There have been reports of chronic overdose in patients taking leflunomide at daily dose up to five times the recommended daily dose and reports of acute overdose in adults or children. There were no adverse events reported in the majority of case reports of overdose. Adverse events were consistent with the safety profile for leflunomide (see ADVERSE REACTIONS). The most frequent adverse events observed were diarrhea, abdominal pain, leukopenia, anemia and elevated liver function tests.

In the event of a significant overdose or toxicity, cholestyramine or charcoal administration is recommended to accelerate elimination (see PRECAUTIONS - General - Need for Drug Elimination).

Studies with both hemodialysis and CAPD (chronic ambulatory peritoneal dialysis) indicate that M1, the primary metabolite of leflunomide, is not dialyzable. (See CLINICAL PHARMACOLOGY – Elimination).

DOSAGE AND ADMINISTRATION

Loading Dose

Due to the long half-life in patients with RA and recommended dosing interval (24 hours), a loading dose is needed to provide steady-state concentrations more rapidly. It is recommended that leflunomide therapy be initiated with a loading dose of one 100 mg tablet per day for 3 days.

Elimination of the loading dose regimen may decrease the risk of adverse events. This could be especially important for patients at increased risk of hematologic or hepatic toxicity, such as those receiving concomitant treatment with methotrexate or other immunosuppressive agents or on such medications in the recent past. (See WARNINGS - Hepatotoxicity).

Maintenance Therapy

Daily dosing of 20 mg is recommended for treatment of patients with RA. A small cohort of patients (n=104), treated with 25 mg/day, experienced a greater incidence of side effects; alopecia, weight loss, liver enzyme elevations. Doses higher than 20 mg/day are not recommended. If dosing at 20 mg/day is not well tolerated clinically, the dose may be decreased to 10 mg daily. Liver enzymes should be monitored and dose adjustments may be necessary (see WARNINGS – Hepatotoxicity). Due to the prolonged half-life of the active metabolite of leflunomide, patients should be carefully observed after dose reduction, since it may take several weeks for metabolite levels to decline.

Monitoring

Hematology parameters and liver enzymes should be monitored (see PRECAUTIONS – Laboratory Tests; WARNINGS – Hepatotoxicity; WARNINGS – Immunosuppression Potential/Bone Marrow Suppression).

HOW SUPPLIED

Leflunomide Tablets, USP in 10 and 20 mg strengths are packaged in bottles.

Strength | Quantity | NDC Number | Description
10 mg | 30 count bottle | 23155-043-03 | White, round bi-convex tablets debossed with “HP 43” on one side and plain on the other.
500 count bottle | 23155-043-05
20 mg | 30 count bottle | 23155-044-03 | White, triangular bi-convex tablets debossed with “HP 44” on one side and plain on the other.
500 count bottle | 23155-044-05

Store at 25°C (77°F); excursions permitted to 15° to 30°C (59° to 86°F) [see USP Controlled Room Temperature]. Protect from light.

Rx only

Manufactured for:

Heritage Pharmaceuticals Inc.

Edison, NJ 08837

And Relabeled By:

Dispensing Solutions Inc.
3000 West Warner Ave
Santa Ana, CA 92704
United States

PACKAGE LABEL.PRINCIPAL DISPLAY PANEL

NDC 68258-2992-03